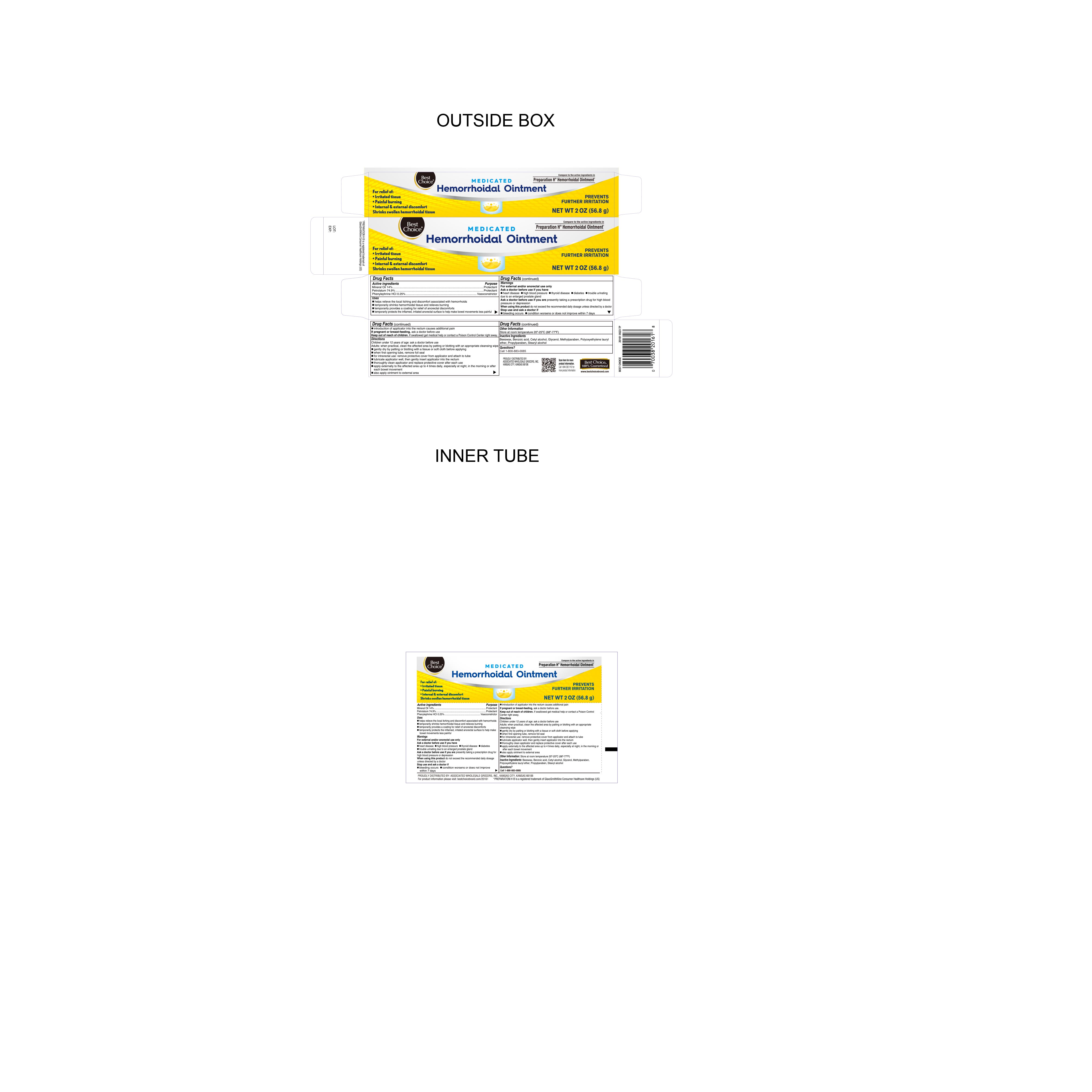 DRUG LABEL: HemorrhoidalOintment
NDC: 69396-133 | Form: OINTMENT
Manufacturer: Trifecta Pharmaceuticals USA LLC
Category: otc | Type: HUMAN OTC DRUG LABEL
Date: 20241218

ACTIVE INGREDIENTS: MINERAL OIL 14 g/100 g; PETROLATUM 74.9 g/100 g; PHENYLEPHRINE HYDROCHLORIDE 0.25 g/100 g
INACTIVE INGREDIENTS: BENZOIC ACID; PROPYLPARABEN; METHYLPARABEN; YELLOW WAX; GLYCERIN; LAURETH-15; STEARYL ALCOHOL; CETYL ALCOHOL

Best Choice Hemorrhoidal Ointment

Active Ingredient

Phenylephrine HCI 0.25%

Purpose

Vasoconstrictor

Active Ingredient

Mineral Oil 14%

Purpose

Protectant

Active Ingredient

Petrolatum 74.9%

Purpose

Protectant

Uses

- Helps relieve the local itching and discomfort associated with hemorrhoids
- Temporarily shrinks hemorrhoidal tissue and relieves burning
- Temporarily provides a coating for relief of anorectal discomforts
- Temporarily profects the inflamed, irritated anorectal surface to help make bowel movements less painful
- Introduction of applicator into the rectum causes additional pain

Warnings

For external and/or anorectal use only

Ask doctor before use if you have

- heart disease
- high blood pressure
- thyroid disease
- diabetes
- trouble urinating due to an enlarged prostate gland

Ask doctor before use if you are presently taking a prescription drug for high blood pressure or depression

Stop Use and Ask Doctor if

- Bleeding occurs
- Condition worsens or does not improve within 7 days

If Pregnant or Breast-Feeding

Ask a doctor before use

Keep out of reach of children

If swallowed get medical help or contact a Poison Control Center right away

When using this product do not exceed the recommended dosage unless directed by a doctor

Directions

Children under 12 years of age: ask a doctor before use.

Adults: when practical, clean the affected area by patting or blotting with an appropriate cleansing wipe

- Gently dry by patting or blotting with a tissue or soft cloth before applying
- When first opening tube, remove foil seal
- For intrarectal use: remove protective cover from applicator and attach to tube
- Lubricate applicator well, then gently insert applicator into rectum
- Thoroughly clean applicator and replace protective cover after each use
- Clean the affected area and pat or dab dry before applying ointment
- Apply externally to the affected area up to 4 times daily, especially at night, in the morning or after each bowel movement
- also apply ointment to external area.

Other Information

- Store at room temperature 20°-25°C (68°-77°F)

Inactive Ingredients

Beeswax, Benzoic Acid, Cetyl alcohol, Glycerol Methylparaben, Polyoxyethylene lauryl ether, Propylparaben, Stearyl alcohol

Questions

Call 1-800-883-0085

Distributed By

Proudly Distributed by

Assocated wholesale grocers inc

kansas city Kansas 66106

Call 1 844 2921112 for product information

www.bestchoicebrand.com

Preparation H is a registered trademark of Glaxosmithkline consumer healthcare holdings US